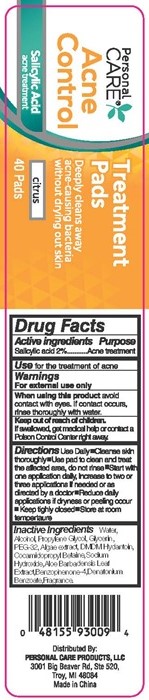 DRUG LABEL: Personal CARE Acne Control
NDC: 29500-9309 | Form: LIQUID
Manufacturer: Personal Care Products
Category: otc | Type: HUMAN OTC DRUG LABEL
Date: 20151109

ACTIVE INGREDIENTS: SALICYLIC ACID 0.025 g/1 1
INACTIVE INGREDIENTS: WATER; ALCOHOL; PROPYLENE GLYCOL; GLYCERIN; PEG-23 GLYCERYL DISTEARATE; NORI; DMDM HYDANTOIN; COCAMIDOPROPYL BETAINE; SODIUM HYDROXIDE; ALOE VERA LEAF; SULISOBENZONE; DENATONIUM BENZOATE

Personal Care® Acne Control

Drug Facts Active ingredients

Salicylic acid 2%

Purpose

Acne treatment

Keep out of reach of children, If swallowed, get medical help or contact a Poison Control Center right away.

Use

for the treatment of acne

Warnings

For external use only

When using this product

avoid contact with eyes. If contact occurs, rinse thoroughly with water.

Directions

Use daily

- Cleanse skin thoroughly
- Use pad to clean and treat the affected area, do not rinse
- Start with one application daily. Increase to two or three applications if needed or as directed by a doctor
- Reduce daily applications if dryness or peeling occur
- Keep tightly closed
- Store at room temperature

Inactive ingredients

Water, Alcohol, propylene Glycol, Glycerin, PEG-23, Algae extract, DMDM Hydantoin, Cocamidopropyl Betadine, Sodium Hydroxide, Aloe Barbadenis Leaf Extract, Benzophenone-4, Denatonium Benzoate, Fragrance

Personal CARE® Acne Control Label

Personal CARE®

Acne Control

Salicylic Acid

acne treatment

Treatment Pads

Deeply Cleans away acne-causing bacteria without drying out skin

citrus

40 pads

Distributed By;

PERSONAL CARE PRODUCTS, LLC

3001 Big Beaver Rd. Ste 520,

Try, MI 48084

Made in China